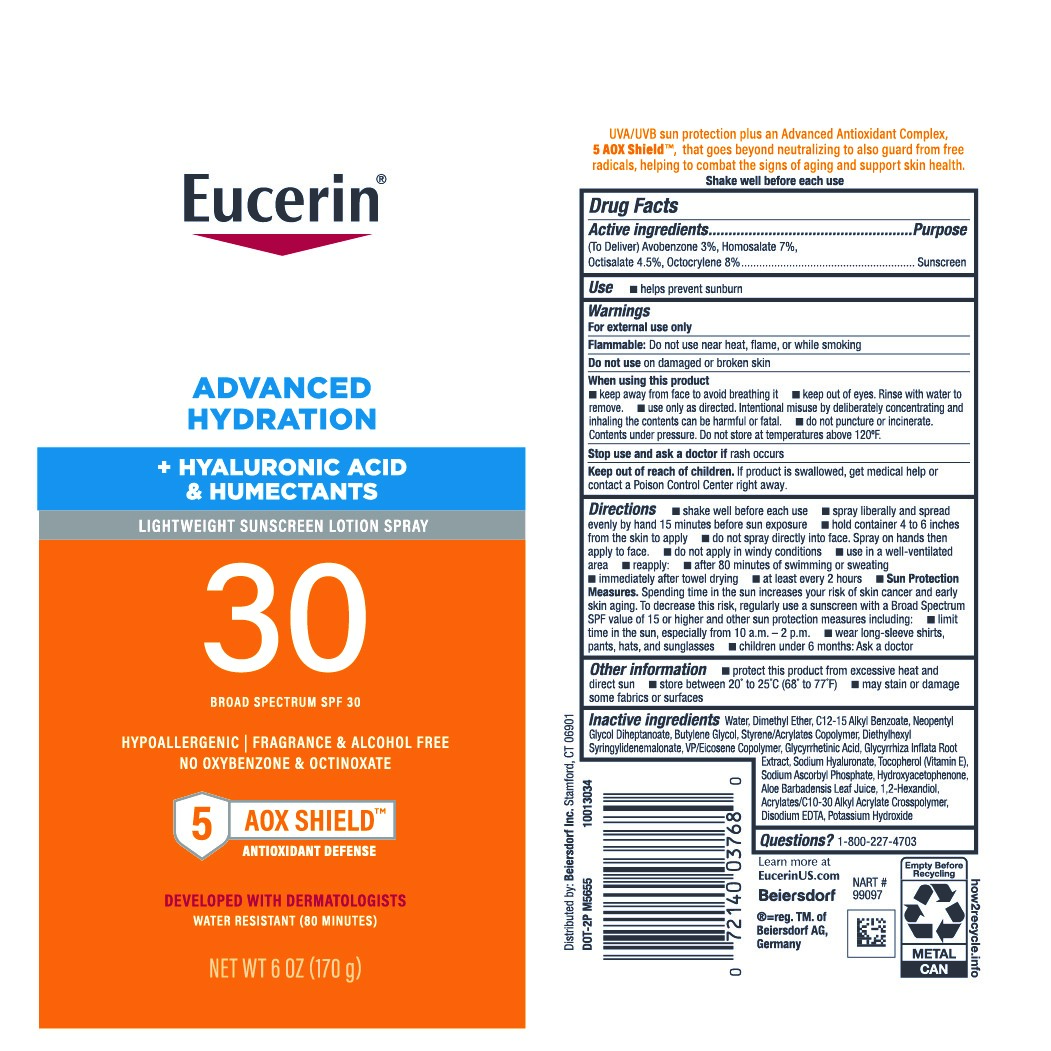 DRUG LABEL: Eucerin Advanced Hydration Sunscreen SPF 30
NDC: 66800-0376 | Form: AEROSOL, SPRAY
Manufacturer: Beiersdorf Inc
Category: otc | Type: HUMAN OTC DRUG LABEL
Date: 20251231

ACTIVE INGREDIENTS: HOMOSALATE 7 g/100 g; OCTISALATE 4.5 g/100 g; OCTOCRYLENE 8 g/100 g; AVOBENZONE 3 g/100 g
INACTIVE INGREDIENTS: POTASSIUM HYDROXIDE; NEOPENTYL GLYCOL DIHEPTANOATE; VINYLPYRROLIDONE/EICOSENE COPOLYMER; ALLANTOIN GLYCYRRHETINIC ACID; TOCOPHEROL; SODIUM ASCORBYL PHOSPHATE; HYDROXYACETOPHENONE; WATER; ALKYL (C12-15) BENZOATE; BUTYLENE GLYCOL; STYRENE/ACRYLAMIDE COPOLYMER (MW 500000); DIETHYLHEXYL SYRINGYLIDENEMALONATE; DIMETHYL ETHER; 1,2-HEXANEDIOL; ACRYLATES/C10-30 ALKYL ACRYLATE CROSSPOLYMER (60000 MPA.S); HYALURONATE SODIUM; GLYCYRRHIZA INFLATA ROOT; ALOE VERA LEAF; DISODIUM EDTA-COPPER

Eucerin Advanced Hydration Lotion Spray SPF 30

Active ingredients

(To Deliver) Avobenzone 3%, Homosalate 7%, Octisalate 4.5%, Octocrylene 8%

Purpose

Sunscreen

Uses

■ helps prevent sunburn

■ if used as directed with other sun protection measures (see Directions), decreases the risk of skin cancer and early skin aging caused by the sun

Warnings

For external use only
Flammable:Do not use near heat, flame, or while smoking

Do not useon damaged or broken skin

WHEN USING

■ keep away from face to avoid breathing it

■ keep out of eyes. Rinse with water to remove.

■ use only as directed. Intentional misuse by deliberately concentrating and inhaling
the contents can be harmful or fatal.

■ do not puncture or incinerate. Contents under pressure. Do not store at temperatures above 120°F.

Stop use and ask a doctor ifrash occurs

Keep out of reach of children.If product is swallowed, get medical help or contact a Poison Control Center right away.

Directions

■ shake well before each use

■ spray liberally and spread evenly by hand 15 minutes before sun exposure

■ hold container 4 to 6 inches from the skin to apply

■ do not spray directly into face. Spray on hands then apply to face.

■ do not apply in windy conditions

■ use in a well-ventilated area

■ reapply:

■ after 80 minutes of swimming or sweating

■ immediately after towel drying

■ at least every 2 hours

■ Sun Protection Measures.Spending time in the sun increases your risk of skin cancer and early skin aging. To decrease this risk, regularly use a sunscreen with a Broad Spectrum SPF value of 15 or higher and other sun protection measures including:

■ limit time in the sun, especially from 10 a.m. – 2 p.m.

■ wear long-sleeve shirts, pants, hats, and sunglasses

■ children under 6 months: Ask a doctor

Other information

■ protect this product from excessive heat and direct sun

■ store between 20° to 25°C (68° to 77°F)

■ may stain or damage some fabrics or surfaces

Inactive ingredients

Water, Dimethyl Ether, C12-15 Alkyl Benzoate, Neopentyl Glycol Diheptanoate, Butylene Glycol, Styrene/Acrylates Copolymer, Diethylhexyl Syringylidenemalonate, VP/Eicosene Copolymer, Glycyrrhetinic Acid, Glycyrrhiza Inflata Root Extract, Sodium Hyaluronate, Tocopherol (Vitamin E), Sodium Ascorbyl Phosphate, Hydroxyacetophenone, Aloe Barbadensis Leaf Juice, 1,2-Hexandiol, Acrylates/C10-30 Alkyl Acrylate Crosspolymer, Disodium EDTA, Potassium Hydroxide

Questions?

1-800-227-4703

PACKAGE LABEL

Eucerin®

Advanced Hydration

+ Hyaluraonic Acid & Humenctants

Lightweight Sunscreen Lotion Spray

30

Broad Spectrum SPF 30

Hypoallergenic | Fragrance & Alcohol Free

No Oxybenzone & Octinoxante

5 AOX Shield Antioxidant Defense

Developed with Dermatologists

Water Resistant (80 Minutes)